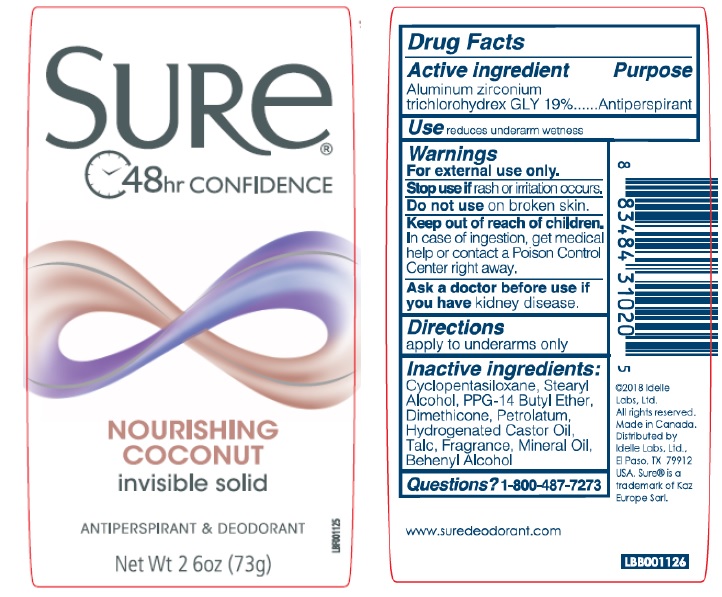 DRUG LABEL: Sure Invisible Solid Nourishing Coconut
NDC: 41595-5547 | Form: STICK
Manufacturer: Idelle Labs, Ltd
Category: otc | Type: HUMAN OTC DRUG LABEL
Date: 20210820

ACTIVE INGREDIENTS: ALUMINUM ZIRCONIUM TRICHLOROHYDREX GLY 19 g/100 g
INACTIVE INGREDIENTS: CYCLOMETHICONE 5; STEARYL ALCOHOL; PPG-14 BUTYL ETHER; DIMETHICONE; PETROLATUM; HYDROGENATED CASTOR OIL; TALC; MINERAL OIL; DOCOSANOL

Sure Invisible Solid Nourishing Coconut

SURe®

48hr CONFIDENCE

NOURISHING
COCONUT

invisible solid

ANTIPERSPIRANT & DEODORANT

Net Wt 2 6oz (73g)

Drug Facts

Active ingredient

Aluminum zirconium trichlorohydrex GLY 19%

Purpose

Antiperspirant

Use

Reduces underarm wetness

Warnings

For external use only.

Stop use if

Rash or irritation occurs.

Do not use

On broken skin.

Keep out of reach of children.

In case of ingestion, get medical help or contact a Poison Control Center right away.

Ask a doctor before use if you have

kidney disease.

Directions

Apply to underarms only

Inactive ingredients:

Cyclopentasiloxane, Stearyl Alcohol, PPG-14 Butyl Ether, Dimethicone, Petrolatum, Hydrogenated Castor Oil, Talc, Fragrance, Mineral Oil, Behenyl Alcohol

Questions?

1-800-487-7273
www.suredeodorant.com
©2018 Idelle Labs, Ltd.
All rights reserved.
Made in Canada.
Distributed by
Idelle Labs, Ltd.,
El Paso, TX 79912 USA.
Sure® is a trademark of Kaz Europe Sarl.